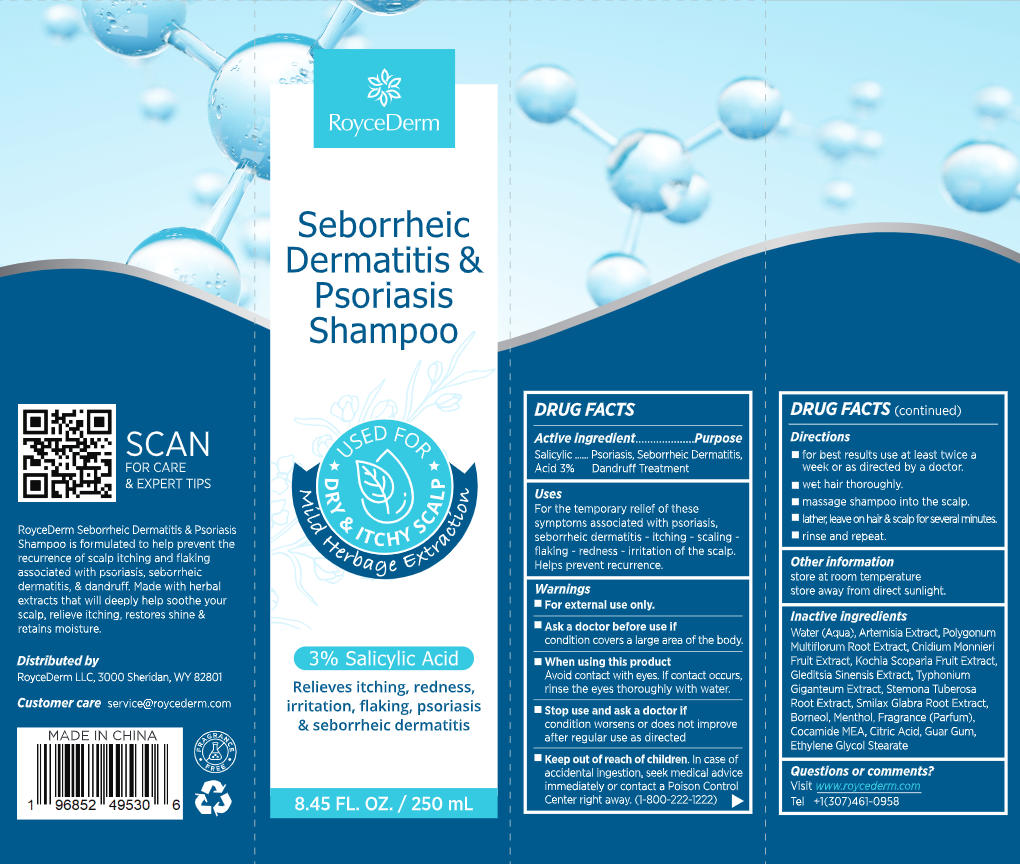 DRUG LABEL: RoyceDerm Seborrheic Dermatitis and Psoriasis shampoo.
NDC: 85424-015 | Form: SHAMPOO
Manufacturer: RoyceDerm LLC
Category: otc | Type: HUMAN OTC DRUG LABEL
Date: 20260130

ACTIVE INGREDIENTS: SALICYLIC ACID 7.5 g/250 g
INACTIVE INGREDIENTS: COCAMIDE MEA; GLYCOL CETEARATE; ARTEMISIA AFRA TOP; REYNOUTRIA MULTIFLORA ROOT OIL; MENTHOL; SMILAX GLABRA WHOLE; BORNEOL; CNIDIUM MONNIERI FRUIT OIL; PARFUMIDINE; STEMONA TUBEROSA ROOT; WATER; SAUROMATUM GIGANTEUM WHOLE; CITRIC ACID; GLEDITSIA SINENSIS FRUIT; BASSIA SCOPARIA FRUIT; GUAR GUM

Initial Drug Listing - RoyceDerm Seborrheic Dermatitis & Psoriasis Shampoo- 85424-015-01

ACTIVE INGREDIENT

Salicylic Acid 3%

PURPOSE

Psoriasis, Seborrheic Dermatitis,Dandruff Treatment

DOSAGE AND ADMINISTRATION

For the temporary relief of theses ymptoms associated with psoriasis,seborrheic dermatitis - itching - scaling -flaking - redness - irritation of the scalp.Helps prevent recurrence.

WARNINGS

For external use only.

ASK DOCTOR

condition covers a large area of the body.

WHEN USING

Avoid contact with eyes. Ifcontact occurs, rinse the eyes thoroughly with water.

STOP USE

condition worsens or does not improve after regular use as directed.

KEEP OUT OF REACH OF CHILDREN

In case of accidental ingestion, seek medical advice immediately or contact a Poison Control Center right away. (1-800-222-1222)

INDICATIONS AND USAGE

- For best results use at least twice a week or as directed by a doctor.
- Wet hair thoroughly.
- Massage shampoo into the scalp.
- Lather, leave on hair & scalp for several minutes.
- Rinse and repeat.

OTHER SAFETY INFORMATION

- Store at room temperature
- Store away from direct sunlight.

INACTIVE INGREDIENT

Water (Aqua), Artemisia Extract, Polygonum Multiflorum Root Extract, Cnidium Monnieri Fruit Extract, Kochia Scoparia Fruit Extract,Gleditsia Sinensis Extract, Typhonium Giganteum Extract, Stemona Tuberosa Root Extract, Smilax Glabra Root Extract,Borneol, Menthol, Fragrance (Parfum),Cocamide MEA, Citric Acid, Guar Gum,Ethylene Glycol Stearate

QUESTIONS

Visit www.roycederm.com

Tel +1(307)461-0958